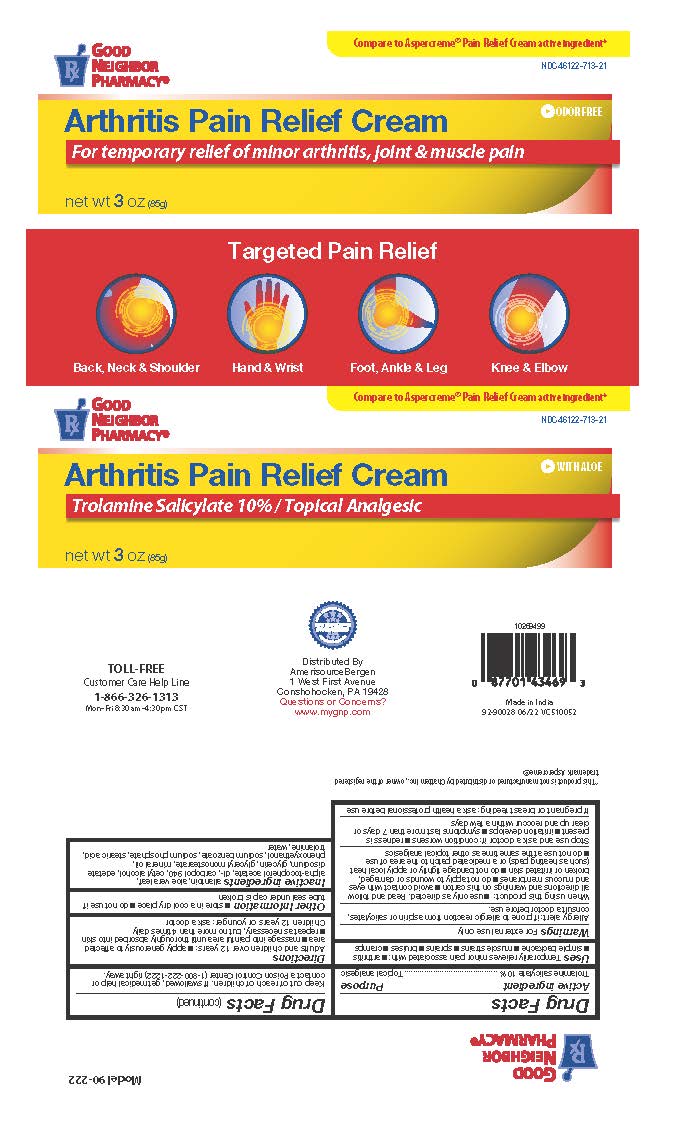 DRUG LABEL: Good Neighbor Pharmacy Arthritis Cream
NDC: 46122-713 | Form: CREAM
Manufacturer: Amerisource Bergen
Category: otc | Type: HUMAN OTC DRUG LABEL
Date: 20241218

ACTIVE INGREDIENTS: TROLAMINE SALICYLATE 10 g/100 g
INACTIVE INGREDIENTS: EDETATE DISODIUM; .ALPHA.-TOCOPHEROL ACETATE, DL-; SODIUM BENZOATE; SODIUM PHOSPHATE; ALOE VERA LEAF; CETYL ALCOHOL; GLYCERIN; MINERAL OIL; CARBOMER 940; STEARIC ACID; TROLAMINE; WATER; GLYCERYL MONOSTEARATE; PHENOXYETHANOL; ALLANTOIN

Good Neighbor Pharmacy Arthritis Cream

Good Neighbor Pharmacy Arthritis Cream

Active ingredient

Trolamine salicylate 10%

Purpose

Topical analgesic

Uses

temporary relieves minor pain associated with:

- arthritis
- simple backache
- muscle strains
- sprains
- bruises
- cramps

Warnings

For external use only

Allergy alert:

If prone to allergic reaction from aspirin or salicylates, consult a doctor before use.

When using this product

- use only as directed. Read and follow all directions and warnings on this carton.
- avoid contact with eyes or mucous membranes
- do not apply to wounds or damaged, broken or irritated skin
- do not bandage tightly or apply local heat (such as heating pads) to the area of use
- do not use at the same time as other topical analgesics

Stop use and ask a doctor if

- condition worsens
- redness is present
- irritation develops
- symptoms persist for more than 7 days or clear up and occur again within a few days

If pregnant or breast-feeding,

ask a health professional before use.

Keep out of reach of children.

If swallowed, get medical help or contact a Poison Control Center (1-800-222-1222) right away.

Directions

adults and children over 12 years:

- apply generously to affected area
- massage into painful area until thoroughly absorbed into skin
- repeat as necessary, but no more than 3 to 4 times daily

children 12 years and younger: ask a doctor

Inactive ingredients

allantoin, aloe vera leaf, alpha-tocopherol acetate, dl-,carbopol 940, cetyl alcohol, edetate disodium, glycerin, glyceryl monostearate, mineral oil, phenoxyethanol, sodium benzoate, sodium phosphate, stearic acid, trolamine, water

Close cap tightly after use.